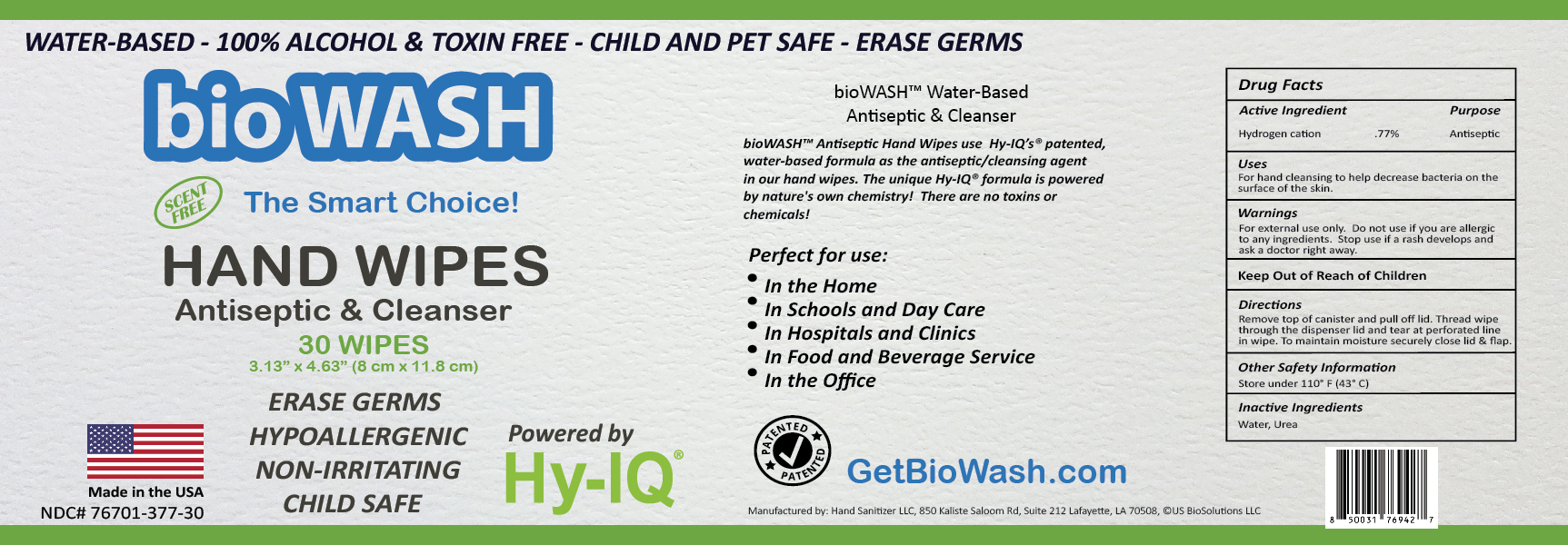 DRUG LABEL: BioWash Hand Wipes
NDC: 76701-377 | Form: CLOTH
Manufacturer: Hand Sanitizer LLC
Category: otc | Type: HUMAN OTC DRUG LABEL
Date: 20210820

ACTIVE INGREDIENTS: HYDROGEN CATION 10 mg/1 mL
INACTIVE INGREDIENTS: UREA 50 mg/1 mL; WATER 940 mg/1 mL

Active Ingredients

Hydrogen Cation .77%

Purpose

Antiseptic Wipe

Uses

For hand sanitizing to help decrease bacteria on the surface of the skin.

Warnings

For external use only. Do not use if you are allergic to any ingredients. Stop use if a rash develops and ask a doctor right away.

Stop use and ask a doctor if skin irritation or rash develops right away.

Keep Out of Reach of Children

Directions

Remove top of canister and pull off lid. Thread wipe through the dispenser lid and tear at perforated line in wipe. To maintain moisture securely close lid and flap.

Other Safety Information

Store under 110º F (43º C)

Inactive Ingredients

Water, Urea